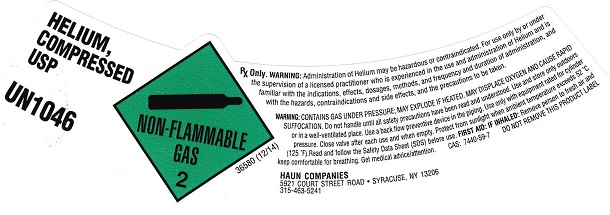 DRUG LABEL: Helium
NDC: 14961-005 | Form: GAS
Manufacturer: Haun Specialty Gases, Inc.
Category: prescription | Type: HUMAN PRESCRIPTION DRUG LABEL
Date: 20251229

ACTIVE INGREDIENTS: HELIUM 990 mL/1 L

Helium

PACKAGE LABEL

HELIUM, COMPRESSED USP UN1046 NON-FLAMMABLE GAS 2
Rx only. WARNING Administration of Helium may be hazardous or contraindicated. For use only by or under the supervision of a licensed practitioner who is experienced in the use and administration of Helium and is familiar with the indications, effects, dosages, methods, and frequency and duration of administration, and with the hazards, contraindications, and side effects and the precautions to be taken. WARNING: CONTAINS GAS UNDER PRESSURE; MAY EXPLODE IF HEATED. MAY DISPLACE OXYGEN AND CAUSE RAPID SUFFOCATION. Do not handle until all safety precautions have been read and understood. Use and store only outdoors or in a well-ventilated place. Use a back flow preventive device in the piping. Use only with equipment rated for cylinder pressure. Close valve after each use and when empty. Protect from sunlight when ambient temperature exceeds 52 degrees C (125 degrees F). Read and follow the Safety Data Sheet (SDS) before use. FIRST AID: IF INHALED: Remove person to fresh air and keep comfortable for breathing. Get medical advice/attention.
CAS 7440-59-7 DO NOT REMOVE THIS PRODUCT LABEL
Net Contents Cubic Feet: Liters:
nexAir
HAUN COMPANIES 5921 COURT STREET ROAD . SYRACUSE, NY 13206 315-463-5241